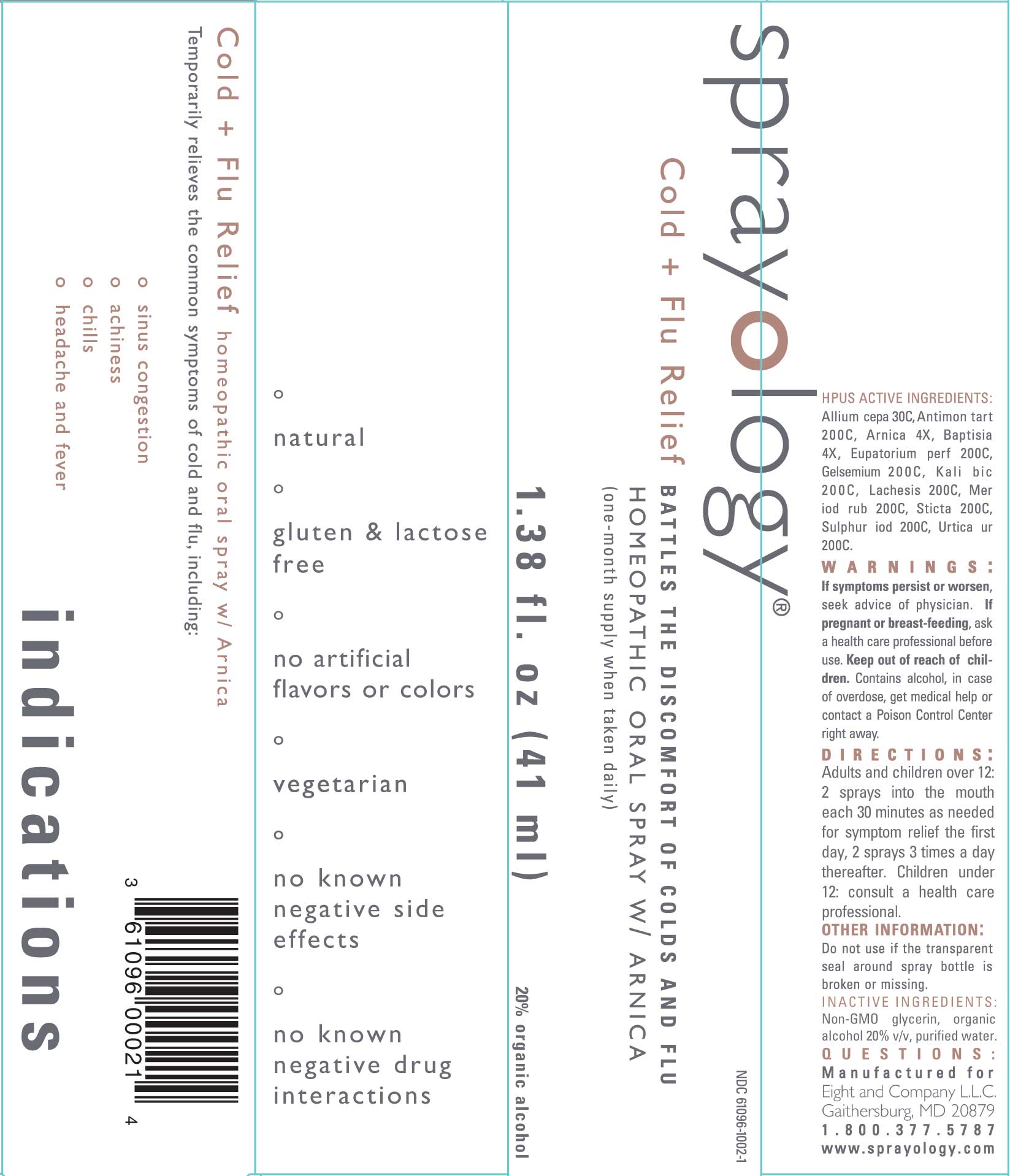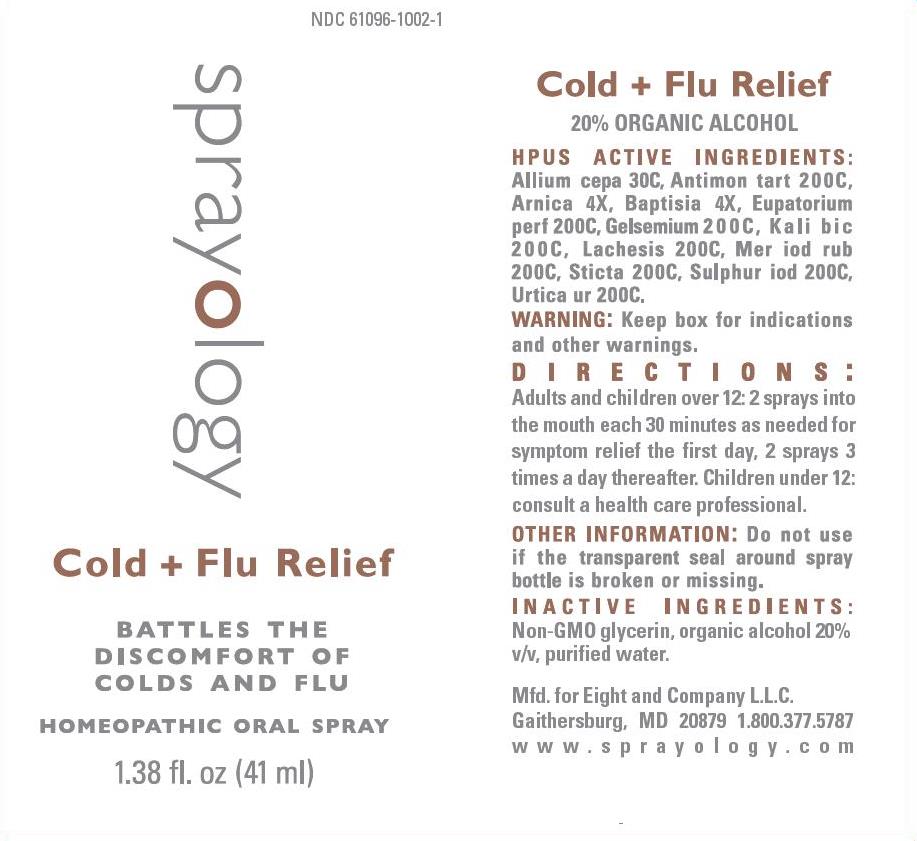 DRUG LABEL: Cold and Flu Relief
NDC: 61096-1002 | Form: LIQUID
Manufacturer: Eight and Company L.L.C
Category: homeopathic | Type: HUMAN OTC DRUG LABEL
Date: 20251222

ACTIVE INGREDIENTS: ONION 30 [hp_C]/41 mL; ANTIMONY POTASSIUM TARTRATE 200 [hp_C]/41 mL; ARNICA MONTANA WHOLE 4 [hp_X]/41 mL; BAPTISIA TINCTORIA ROOT 4 [hp_X]/41 mL; EUPATORIUM PERFOLIATUM FLOWERING TOP 200 [hp_C]/41 mL; GELSEMIUM SEMPERVIRENS ROOT 200 [hp_C]/41 mL; POTASSIUM DICHROMATE 200 [hp_C]/41 mL; LACHESIS MUTA VENOM 200 [hp_C]/41 mL; MERCURIC IODIDE 200 [hp_C]/41 mL; LOBARIA PULMONARIA 200 [hp_C]/41 mL; SULFUR IODIDE 200 [hp_C]/41 mL; URTICA URENS WHOLE 200 [hp_C]/41 mL
INACTIVE INGREDIENTS: GLYCERIN; ALCOHOL; WATER

Cold and Flu Relief

ACTIVE INGREDIENTS:

Allium cepa 30C, Antimon tart 200C, Arnica 4X, Baptisia 4X, Eupatorium perf 200C, Gelsemium 200C, Kali bic 200C, Lachesis 200C, Merc iod rub 200C, Sticta 200C, Sulphur iod 200C, Urtica ur 200C.

WARNINGS:

If symptoms persist or worsen, seek advice of physician. If pregnant or breast-feeding, ask a health care professional before use. Keep out of reach of children. Contains alcohol, in case of overdose, get medical help or contact a Poison Control Center right away.

KEEP OUT OF REACH OF CHILDREN:

Contains alcohol, in case of overdose, get medical help or contact a Poison Control Center right away.

INDICATIONS:

Temporarily relieves the common symptoms of cold and flu, including:

- sinus congestion
- achiness
- chills
- headache and fever

º Natural

º Gluten & Lactose free

º No artificial flavors or colors

º Vegetarian

º No known negative side effects

º No known negative drug interactions

DIRECTIONS:

Adults and children over 12: 2 sprays into the mouth each 30 minutes as needed for symptom relief the first day, 2 sprays 3 times a day thereafter.Children under 12: consult a health care professional.

OTHER INFORMATION:

Do not use if the transparent seal around spray bottle is broken or missing.

INACTIVE INGREDIENTS:

Non-GMO glycerin, organic alcohol 20% v/v, purified water.

PURPOSE:

Temporarily relieves the common symptoms of cold and flu, including:

- sinus congestion
- achiness
- chills
- headache and fever

º Natural

º Gluten & Lactose free

º No artificial flavors or colors

º Vegetarian

º No known negative side effects

º No known negative drug interactions

QUESTIONS:

Manufactured for

Eight and Company L.L.C.

Gaithersburg, MD 20879

1.800.377.5787

www.sprayology.com

PACKAGE LABEL DISPLAY:

NDC 61096-1002-1

sprayology

Cold + Flu Relief

BATTLES THE

DISCOMFORT OF

COLDS AND FLU

HOMEOPATHIC ORAL SPRAY

1.38 fl.oz (41 ml)